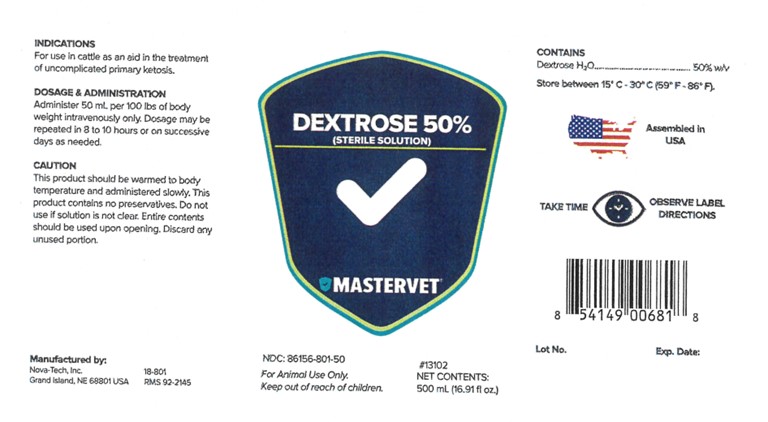 DRUG LABEL: Dextrose 50% Solution
NDC: 86156-801 | Form: INJECTION, SOLUTION
Manufacturer: MasterVet
Category: animal | Type: OTC ANIMAL DRUG LABEL
Date: 20221230

ACTIVE INGREDIENTS: DEXTROSE MONOHYDRATE 50 g/100 mL

Dextrose 50% Solution

Dosage And Administration:

Administer 50 mL per 100 lbs body weight intravenously only. Dosage may be repeated in 8 to 10 hours or on successive days as needed.

Indications

For use in cattle as an aid in the treatment of uncomplicated primary ketosis.

Caution:

This product should be warmed to body temperature and administered slowly. This product contains no preservatives. Do not use if solution is not clear. Entire contents should be used opening. Discard any unused portion.

GENERAL PRECAUTIONS

FOR ANIMAL USE ONLY.
KEEP OUT OF REACH OF CHILDREN.

Contains

Dextrose H2O................................................50% w/v

STORAGE AND HANDLING

Store between 15°C-30°C (59°F-86°F).

GENERAL PRECAUTIONS

TAKE TIME OBSERVE LABEL DIRECTIONS

INFORMATION FOR OWNERS/CAREGIVERS

Manufactured by:

Nova-Tech, Inc.

Grand Island, NE 68801 USA

18-801

RMS 92-2145

NDC# 86156-801-50

Dextrose 50% Solution

Sterile Solution

MasterVet

#13102

Net Contents:

500 mL (16.91 fl oz)

Assembled in USA

Lot No. Exp. Date